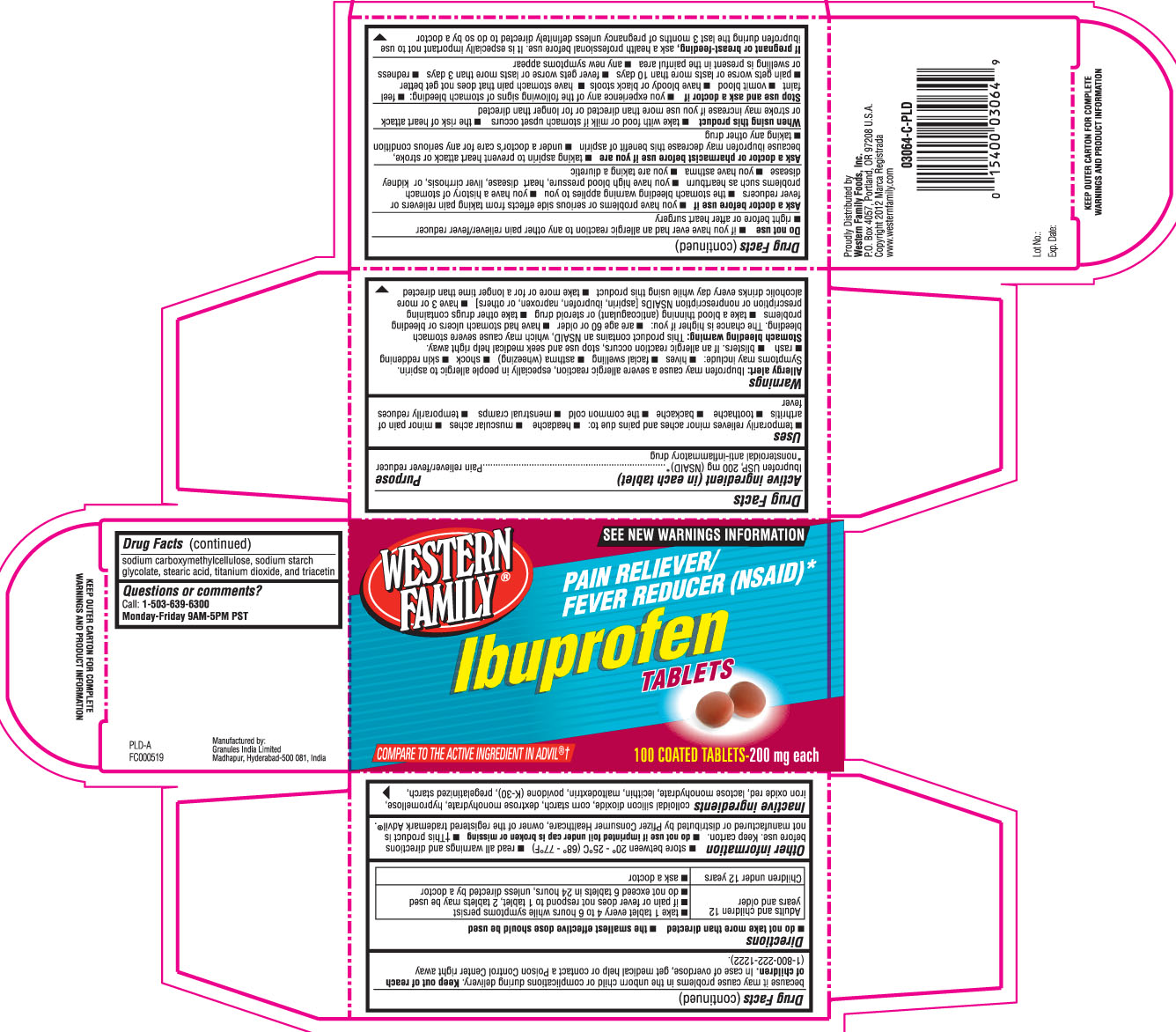 DRUG LABEL: Ibuprofen
NDC: 55312-218 | Form: TABLET
Manufacturer: Western Family Foods, Inc.
Category: otc | Type: HUMAN OTC DRUG LABEL
Date: 20121009

ACTIVE INGREDIENTS: IBUPROFEN 200 mg/1 1
INACTIVE INGREDIENTS: SILICON DIOXIDE; STARCH, CORN; DEXTROSE MONOHYDRATE; HYPROMELLOSES; FERRIC OXIDE RED; LACTOSE MONOHYDRATE; EGG PHOSPHOLIPIDS; MALTODEXTRIN; POVIDONES; STARCH, CORN; CARBOXYMETHYLCELLULOSE SODIUM; SODIUM STARCH GLYCOLATE TYPE A CORN; STEARIC ACID; TITANIUM DIOXIDE; TRIACETIN

DRUG FACTS

Active Ingredient (in each tablet)

Ibuprofen USP, 200 mg (NSAID)*

*nonsteroidal anti-inflammatory drug

Purpose

Pain Reliever/ Fever Reducer

Uses

- temporarily relieves minor aches and pains due to:
  - Headache
  - muscular aches
  - minor pain of arthritis
  - toothache
  - backache
  - the common cold
  - menstrual cramps
  - temporarily reduces fever

Warnings

Allergy alert: Ibuprofen may cause a severe allergic reaction, especially in people allergic to aspirin. Symptoms may include:

- hives
- facial swelling
- asthma (wheezing)
- shock
- skin reddening
- rash
- blisters

If an allergic reaction occurs, stop use an seek medical help right away.

Stomach bleeding warning: This product contains a nonsteroidal anti-inflammatory drug (NSAID) which may cause severe stomach bleeding. The chance are higher if you:

- are age 60 or oder
- have had stomach ulders or bleeding problems
- take blood thinning (anticoagulant) or steroid drug
- take other drugs containing prescritpion or non-prescription NSAIDs (aspirin, ibuprofen, naproxen, or others)
- have 3 or more alcoholic drinks everyday while using this prdouct
- take more or for a longer time than directed.

Do not use

- if you ever had an allergic reaction to any other pain reliever/fever reducer
- right before or after heart surgery

Ask a doctor before use if

- you have problems or serious side effects from taking pain relievers or fever reducers
- the stomach bleeding warning applies to you
- you have a history of stomach problems such as heartburn
- you have high blood pressure, heart disease, liver cirrhosis, or kidney disease
- you have asthma
- you are taking a diuretic.

Ask a doctor or pharmacist before use if you are

- taking aspirin to prevent heart attack or stroke, because ibuprofen may decrease this benefit of aspirin
- under a doctor's care for any serious condition
- taking any other drug.

When using this product

- take with food or milk if stomach upset occurs
- the risk of heart attack or stroke may increase if you use more than directed or for longer than directed.

Stop use and ask a doctor if

- You experience any of the following signs of stomach bleeding:
  - feel faint
  - vomit blood
  - have bloody or black stools
  - have stomach pain that does not bet better
  - Pain gets worse or last more than 10 days
  - Fever gets worse or last more than 3 days
  - Redness or swelling is present in the painful area
  - Any new symptoms appear

If pregnant or breast-feeding,

ask a health professional before use. It is especially important not to use ibuprofen druing the last 3 months of pegnancy unless defintely directed to do so by a doctor because it may cause problems in the unborn child or complications during delivery.

Keep out of reach of children.

In case of overdose, get medical help or contact a Poison Control Center right away (1-800-222-1222)

Directions

- do not take more than directed
- the smallest effective dose should be used

Adults and children 12 years and older | - take 1 tablet every 4 to 6 hours while symptoms persist - if pain or fever does not respond to 1 tablet, 2 tablets may be used - do not exceed 6 tablets in 24 hours, unless directed by a doctor
children under 12 years | - ask a doctor

Other information

- store between 20o- 25o C (68o- 77o F)
- read all warnings and directions before use. Keep carton
- do not use if imprinted foil under cap is broken or missing
- †This product is not manufactured or distributed by Pfizer consumer healthcare, owner of the registered trademark Advil®

Inactive Ingredients

colloidal silicon dioxide, corn starch, dextrose monohydrate, hypromellose, iron oxide red, lactose monohydrate, lecithin, maltodextrin, povidone (K-30), pregelatinized starch, sodium carboxymethylcellulose, sodium starch glycolate, stearic acid, titanium dioxide, and triacetin

Questions or comments?

Call: 1-503-639-6300 Monday- Friday 9AM-5PM PST

Principal Display Panel

Compare to the active ingredient in ADVIL®†

SEE NEW WARNINGS INFORMATION

Ibuprofen Tablets

Pain Reliever/ Fever Reducer (NSAID)*

Proudly distributed by Western family foods, Inc.

PO Box 4057, Portland, OR 97208 USA

www.westernfamily.com

Manufactured by:

Granules India limited

Madhapur, Hyderabad- 500081, India

KEEP OUTER CARTON FOR COMPLETE WARNINGS AND PRODUCT INFORMATION

Product Label

Ibuprofen tablets 200 mg tablets